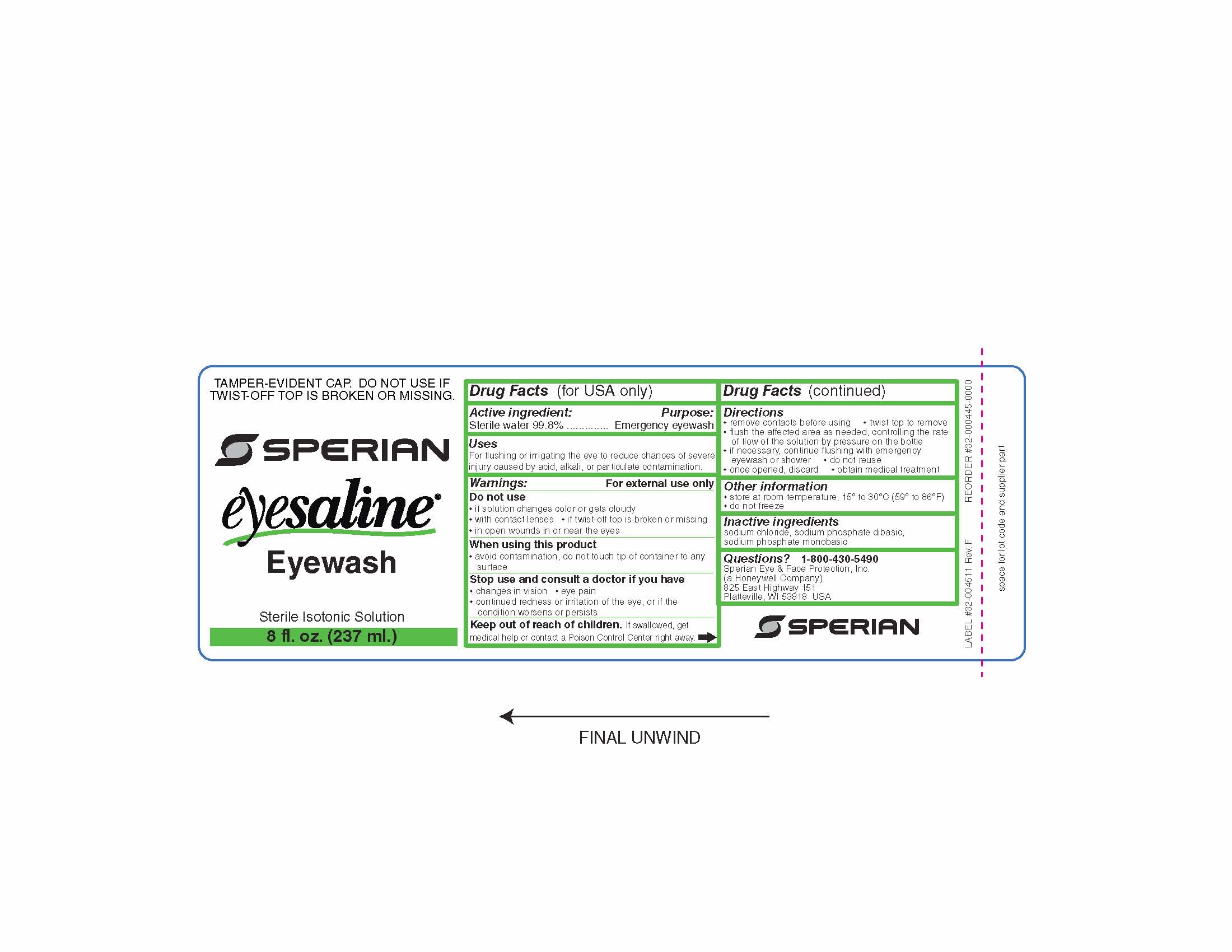 DRUG LABEL: Sperian Eyesaline Eyewash
NDC: 64809-101 | Form: LIQUID
Manufacturer: Sperian Eye & Face Protection Inc
Category: otc | Type: HUMAN OTC DRUG LABEL
Date: 20110907

ACTIVE INGREDIENTS: WATER 99.8 mL/100 mL
INACTIVE INGREDIENTS: SODIUM CHLORIDE; SODIUM PHOSPHATE, MONOBASIC, MONOHYDRATE; SODIUM PHOSPHATE, DIBASIC ANHYDROUS

Sperian Eyesaline Eyewash

Active ingredient

Water 99.8%

Purpose

Emergency eyewash

Uses

- for flushing or irrigating the eye to reduce chances of severe injury caused by acid, alkali, or particulate contamination.

Warnings

For external use only

Do not use

- if solution changes color or gets cloudy
- with contact lenses
- if twist-off top is broken or missing
- in open wounds in or near the eyes

When using this product

- avoid contamination, do not touch tip of container to any surface

When using this product

- avoid contamination, do not touch tip of container to any surface

Stop use and consult a doctor if you have

- changes in vision
- eye pain
- continued redness or irritation of the eye, or if the condition worsens or persists

Keep out of reach of children.

If swallowed, get medical help or contact a Poison Control Center right away.

Directions

- remove contacts before using
- twist top to remove
- flush the affected eye as needed, controlling the rate of flow of the solution by pressure on the bottle
- if necessary, continue flushing with emergency eyewash or shower
- do not reuse
- once opened, discard
- obtain medical treatment

Other information

- store at room temperature, 15o to 30o C (59o to 86o F)
- do not freeze

Inactive ingredients

sodium chloride, sodium phosphate dibasic, sodium phosphate monobasic

Questions?

1-800 - 430-5490
Sperian Eye and Face Protection, Inc.
(a Honeywell Company)
825 East Highway 151
Platteville, WI 53818 USA